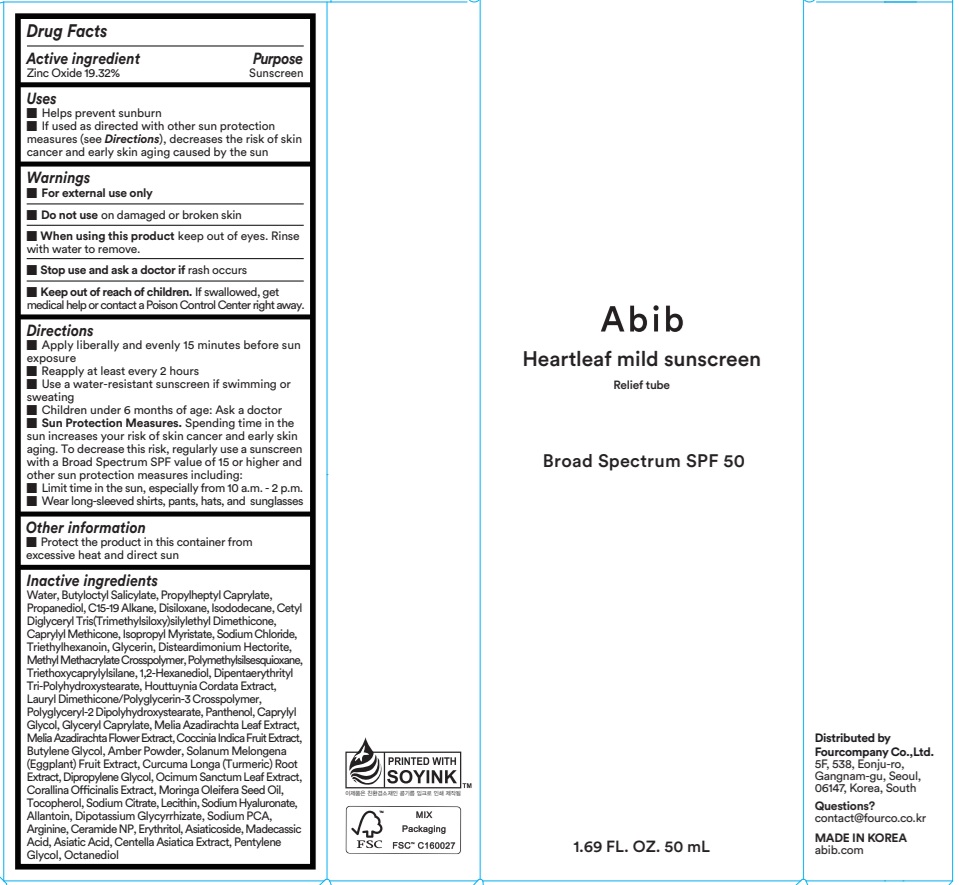 DRUG LABEL: Abib Heartleaf mild sunscreen Relief tube
NDC: 73676-217 | Form: CREAM
Manufacturer: FOURCOMPANY CO., LTD.
Category: otc | Type: HUMAN OTC DRUG LABEL
Date: 20250507

ACTIVE INGREDIENTS: ZINC OXIDE 19.32 g/100 mL
INACTIVE INGREDIENTS: SODIUM CHLORIDE; TRIETHYLHEXANOIN; TRIETHOXYCAPRYLYLSILANE; 1,2-HEXANEDIOL; WATER; ISODODECANE; HOUTTUYNIA CORDATA FLOWERING TOP; BUTYLOCTYL SALICYLATE; CETYL DIGLYCERYL TRIS(TRIMETHYLSILOXY)SILYLETHYL DIMETHICONE (950 MM2/S); DIPENTAERYTHRITYL TRI-POLYHYDROXYSTEARATE; C15-19 ALKANE; CAPRYLYL METHICONE; ISOPROPYL MYRISTATE; PROPANEDIOL; DISILOXANE; DISTEARDIMONIUM HECTORITE; GLYCERIN; POLYGLYCERYL-2 DIPOLYHYDROXYSTEARATE; PROPYLHEPTYL CAPRYLATE

Active ingredient(s)

Zinc Oxide 19.32%

Purpose

Sunscreen

INDICATIONS AND USAGE

Use(s)

■ Helps prevent sunburn

■ If used as directed with other sun protection measures (see Directions), decreases the risk of skin cancer and early skin aging caused by the sun

Warnings

■ For external use only

■ Do not use on damaged or broken skin

■ When using this product keep out of eyes. Rinse with water to remove.

■ Stop use and ask a doctor if rash occurs

■ Keep out of reach of children, If swallowed, get medical help or contact a Poison Control Center right away.

Keep out of reach of children, If swallowed, get medical help or contact a Poison Control Center right away.

Directions

■ Apply liberally and evenly 15 minutes before sun exposure

■ Reapply at least every 2 hours

■ Use a water-resistant sunscreen if swimming or sweating

■ Children under 6 months of age: Ask a doctor

■ Sun Protection Measures. Spending time in the sun increases your risk of skin cancer and early skin aging. To decrease this risk, regularly use a sunscreen with a Broad Spectrum SPF value of 15 or higher and other sun protection measures including:

■ Limit time in the sun, especially from 10 a.m. ‒ 2 p.m.

■ Wear long-sleeved shirts, pants, hats, and sunglasses

Other Information

■ Protect the product in this container from excessive heat and direct sun

Questions

■ contact@fourco.co.kr

Inactive ingredients

Water, Butyloctyl Salicylate, Propylheptyl Caprylate, Propanediol, C15-19 Alkane, Disiloxane, Isododecane, Cetyl Diglyceryl Tris(Trimethylsiloxy)silylethyl Dimethicone, Caprylyl Methicone, Isopropyl Myristate, Sodium Chloride, Triethylhexanoin, Glycerin, Disteardimonium Hectorite, Methyl Methacrylate Crosspolymer, Polymethylsilsesquioxane, Triethoxycaprylylsilane, 1,2-Hexanediol, Dipentaerythrityl Tri-Polyhydroxystearate, Houttuynia Cordata Extract, Lauryl Dimethicone/Polyglycerin-3 Crosspolymer, Polyglyceryl-2 Dipolyhydroxystearate, Panthenol, Caprylyl Glycol, Glyceryl Caprylate, Melia Azadirachta Leaf Extract, Melia Azadirachta Flower Extract, Coccinia Indica Fruit Extract, Butylene Glycol, Amber Powder, Solanum Melongena (Eggplant) Fruit Extract, Curcuma Longa (Turmeric) Root Extract, Dipropylene Glycol, Ocimum Sanctum Leaf Extract, Corallina Officinalis Extract, Moringa Oleifera Seed Oil, Tocopherol, Sodium Citrate, Lecithin, Sodium Hyaluronate, Allantoin, Dipotassium Glycyrrhizate, Sodium PCA, Arginine, Ceramide NP, Erythritol, Asiaticoside, Madecassic Acid, Asiatic Acid, Centella Asiatica Extract, Pentylene Glycol, Octanediol